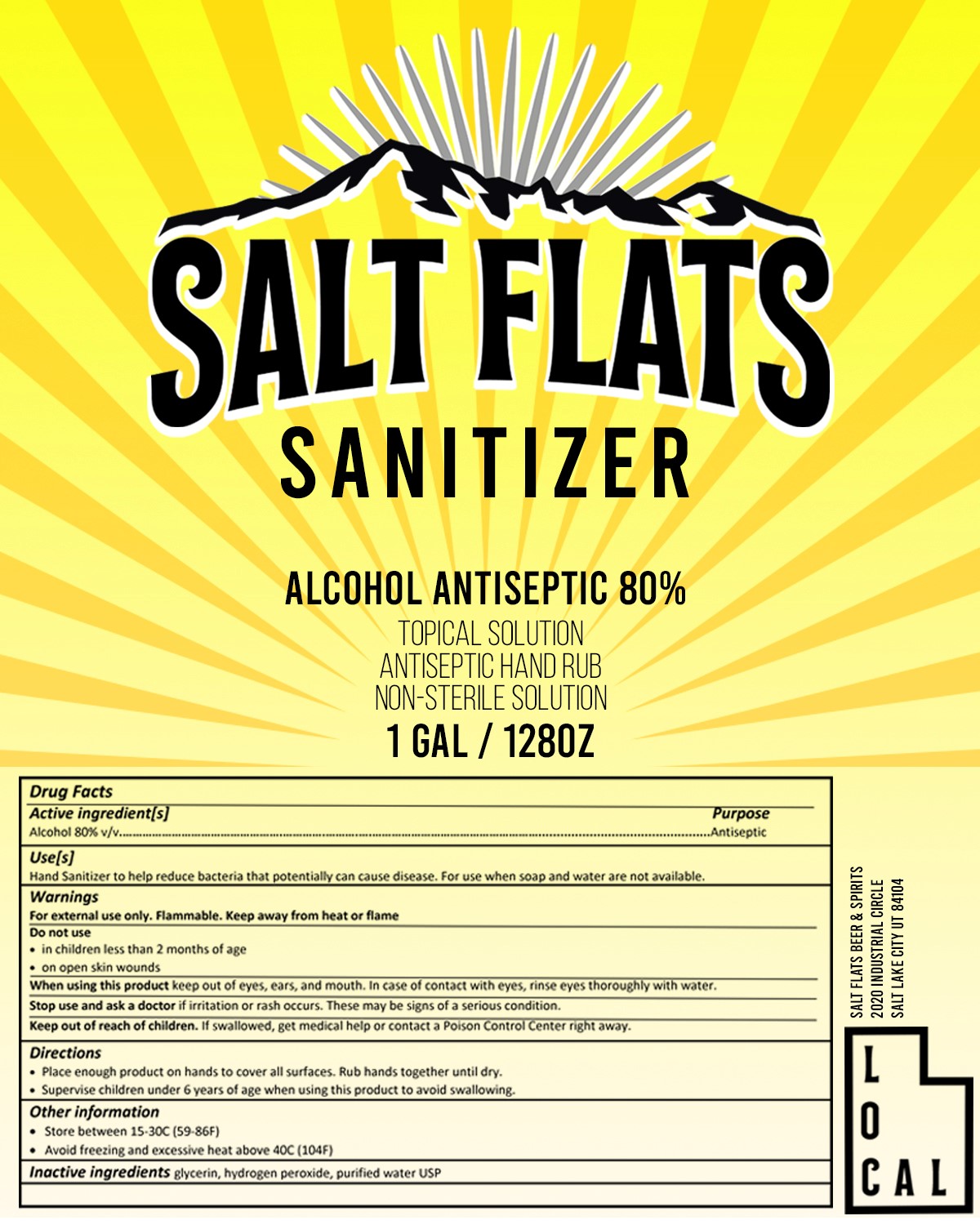 DRUG LABEL: Salt Flats Sanitizer
NDC: 74012-411 | Form: LIQUID
Manufacturer: Salt Flats Spirits
Category: otc | Type: HUMAN OTC DRUG LABEL
Date: 20200325

ACTIVE INGREDIENTS: ALCOHOL 0.8 mL/1 mL
INACTIVE INGREDIENTS: GLYCERIN 0.0145 mL/1 mL; WATER 0.18425 mL/1 mL; HYDROGEN PEROXIDE 0.00125 mL/1 mL

Hand Sanitzer

Use(s)

Hand Sanitizer to help reduce bacteria that potentially can cause disease. FOr use when soap and water are not available.

WARNINGS

For external use only. Flammable. Keep away from heat or flame

Do not use

- in children less than 2 months of age
- on open skin wounds

INDICATIONS AND USAGE

Keep out of eyes, ears, and mouth. Incase of contact with eyes, rinse eyes thoroughly with water.

ASK DOCTOR

if irritiation or rash occurs. These may be signs of a serious condition.

KEEP OUT OF REACH OF CHILDREN

If swollowed, get medical help or contact a poson control center right away.

STORAGE AND HANDLING

Store between 15-30c (59-86F)

Avoid freezing and excessive heat above 40 C (104F)

INACTIVE INGREDIENT

glycerin, hydrogen peroxide, purified water USP

Directions

- Place enough product on hands to cover all surfaces. Rub hands together until dry.
- Supervise children under 6 years of age when using this product to avoid swallowing.